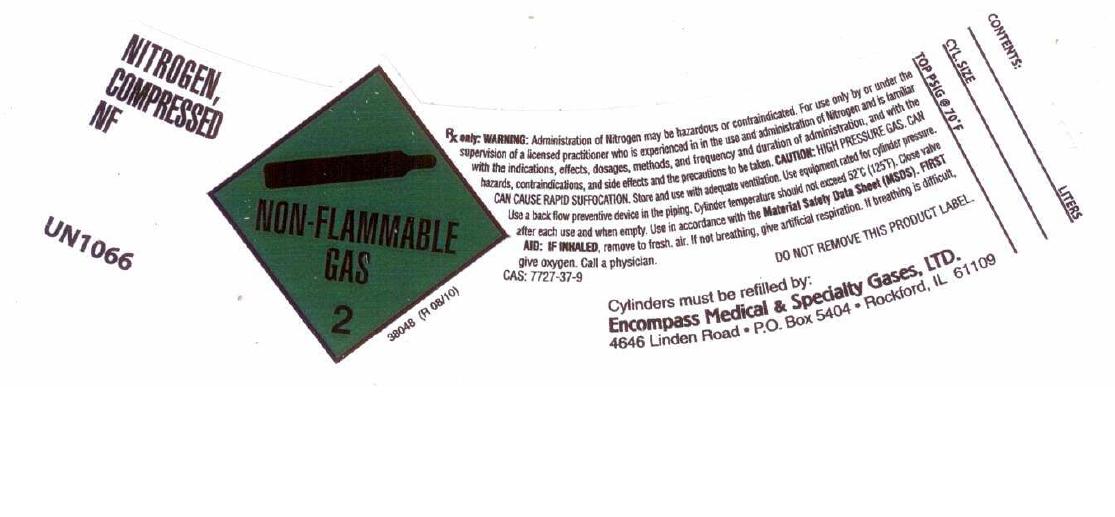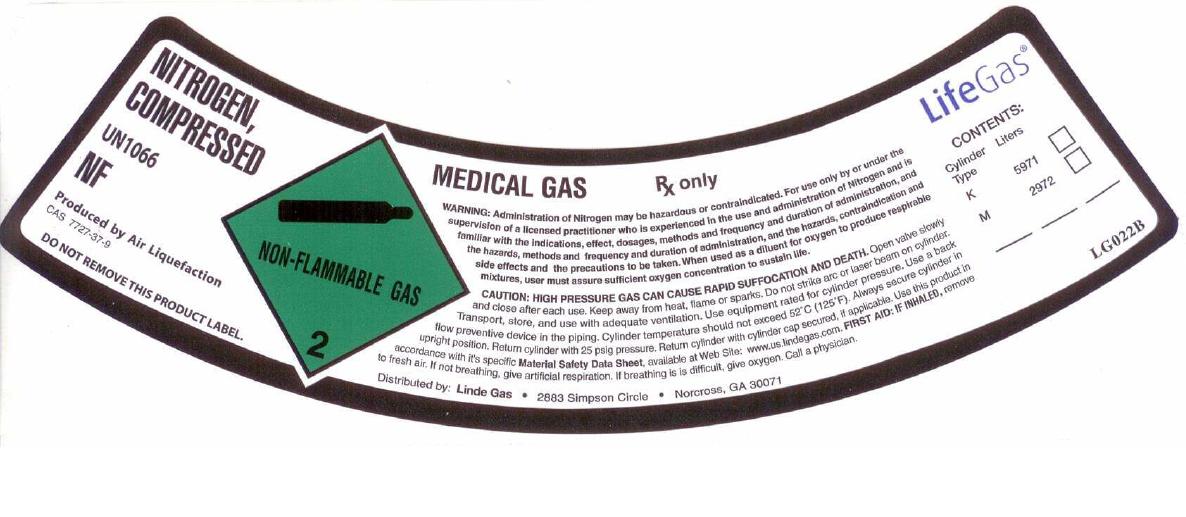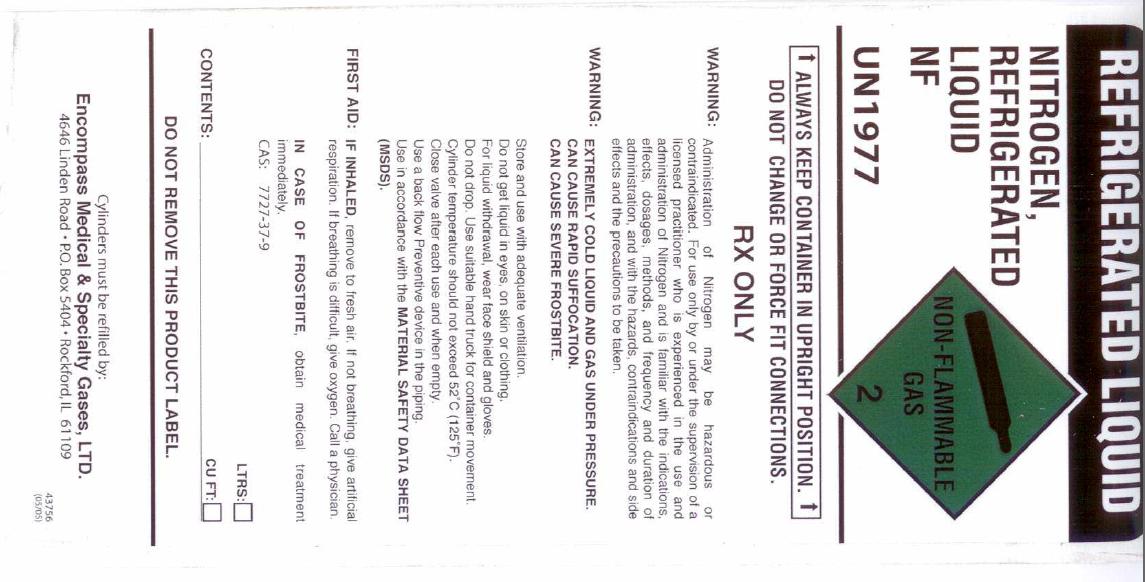 DRUG LABEL: Nitrogen
NDC: 48883-002 | Form: GAS
Manufacturer: Encompass Medical & Specialty Gases, Ltd.
Category: prescription | Type: HUMAN PRESCRIPTION DRUG LABEL
Date: 20101126

ACTIVE INGREDIENTS: Nitrogen 990 mL/1 L

Nitrogen Label

PACKAGE LABEL

NITROGEN, COMPRESSED NF UN1066
NON-FLAMMABLE GAS 2 38048 (R 08/10)
Rx only. WARNING: Administration of Nitrogen may be hazardous or contraindicated. For use only by or under supervision of a licensed practitioner who is experienced in the use and administration of Nitrogen and is familiar with the indications, effects, dosages, methods, and frequency and duration of administration, and with the hazards, contraindications, and side effects and the precautions to be taken. CAUTION: HIGH PRESSURE GAS. CAN CAUSE RAPID SUFFOCATION. Store and use with adequate ventilation. Use equipment rated for cylinder pressure. Use a back flow preventive device in the piping. Cylinder temperatures should not exceed 52C (125F). Close valve after each use and when empty. Use in accordance with the Material Safety Data Sheet (MSDS). FIRST AID: IF INHALED, remove to fresh air. If not breathing, give artificial respiration. If breathing is difficult, give oxygen. Call a physician. CAS: 7727-37-9
DO NOT REMOVE THIS PRODUCT LABEL.
Cylinders must be refilled by:
Encompass Medical and Specialty Gases, LTD. 4646 Linden Road P.O. Box 5404 Rockford, IL 61109
CONTENTS: LITERS CYL. SIZE TOP PSIG at 70 F

PACKAGE LABEL

NITROGEN, COMPRESSED UN1066 NF
Produced by Air Liquefaction
CAS: 7727-37-9 DO NOT REMOVE THIS PRODUCT LABEL.
NON-FLAMMABLE GAS 2
MEDICAL GAS
Rx only. WARNING: Administration of Nitrogen may be hazardous or contraindicated. For use only by or under supervision of a licensed practitioner who is experienced in the use and administration of Nitrogen and is familiar with the indications, effects, dosages, methods, and frequency and duration of administration, and with the hazards, contraindications, and side effects and the precautions to be taken. When used as a diluent for oxygen to produce respirable mixtures, user must assure sufficient oxygen concentration to sustain life.
CAUTION: HIGH PRESSURE GAS. CAN CAUSE RAPID SUFFOCATION AND DEATH. Open valve slowly and close after each use. Keep away from heat, flame or sparks. Do not strike arc or laser beam on cylinder. Transport, store and use with adequate ventilation. Use equipment rated for cylinder pressure. Use a back flow preventive device in the piping. Cylinder temperatures should not exceed 52C (125F). Always secure cylinder in upright position. Return cylinder with 25 psig pressure. Return cylinder with cylinder cap secured, if applicable. Use this product in accordance with the Material Safety Data Sheet, available at Web Site: www.us.lindegas.com. FIRST AID: IF INHALED, remove to fresh air. If not breathing, give artificial respiration. If breathing is difficult, give oxygen. Call a physician.
Distributed by: Linde Gas 2883 Simpson Circle Norcross, GA 30071
LifeGas
Contents: Cylinder Type K M
Liters 5971 2972
LG022B

PACKAGE LABEL

REFRIGERATED NITROGEN
NITROGEN, REFRIGERATED LIQUID NF UN1977
NON-FLAMMABLE GAS 2
ALWAYS KEEP CONTAINER IN UPRIGHT POSITION. DO NOT CHANGE OR FORCE FIT CONNECTIONS.
Rx only. WARNING: Administration of Nitrogen may be hazardous or contraindicated. For use only by or under supervision of a licensed practitioner who is experienced in the use and administration of Nitrogen and is familiar with the indications, effects, dosages, methods, and frequency and duration of administration, and with the hazards, contraindications, and side effects and the precautions to be taken.
WARNING: EXTREMELY COLD LIQUID AND GAS UNDER PRESSURE. CAN CAUSE RAPID SUFFOCATION. CAN CAUSE FROSTBITE. Store and use with adequate ventilation. Do not get liquid in eyes, on skin, or clothing. For liquid withdrawal, wear fae shield and gloves. Do not drop. Use suitable hand truck for container movement. Cylinder temperatures should not exceed 52C (125F). Close valve after each use and when empty. Use a back flow preventive device in the piping. Use in accordance with the Material Safety Data Sheet (MSDS). FIRST AID: IF INHALED, remove to fresh air. If not breathing, give artificial respiration. If breathing is difficult, give oxygen. Call a physician. IN CASE OF FROSTBITE, obtain medical treatment immediately.
CAS: 7727-37-9
CONTENTS: LTRS: CU. FT:
DO NOT REMOVE THIS PRODUCT LABEL.
Cylinders must be refilled by:
Encompass Medical and Specialty Gases, LTD. 4646 Linden Road P.O. Box 5404 Rockford, IL 61109
43756 (05/05)